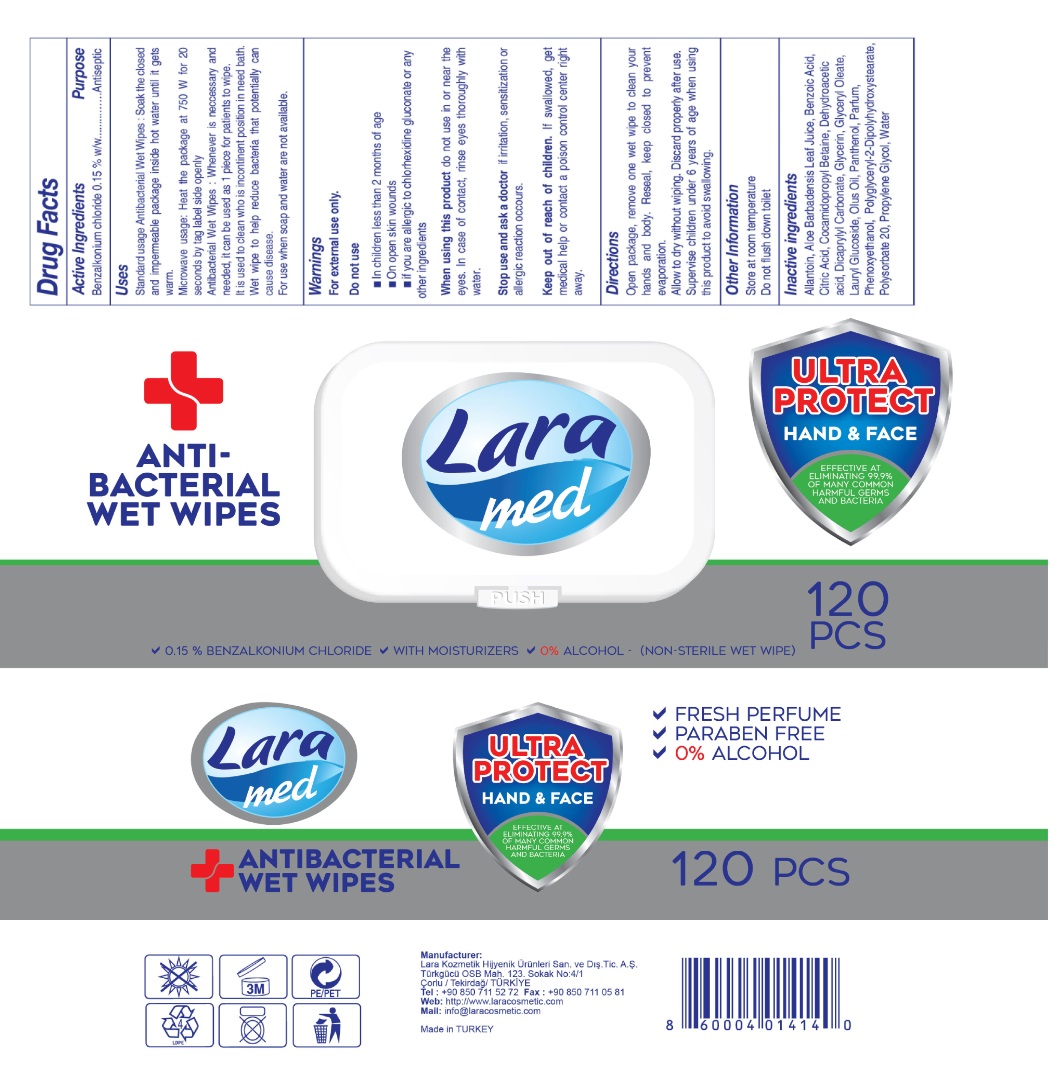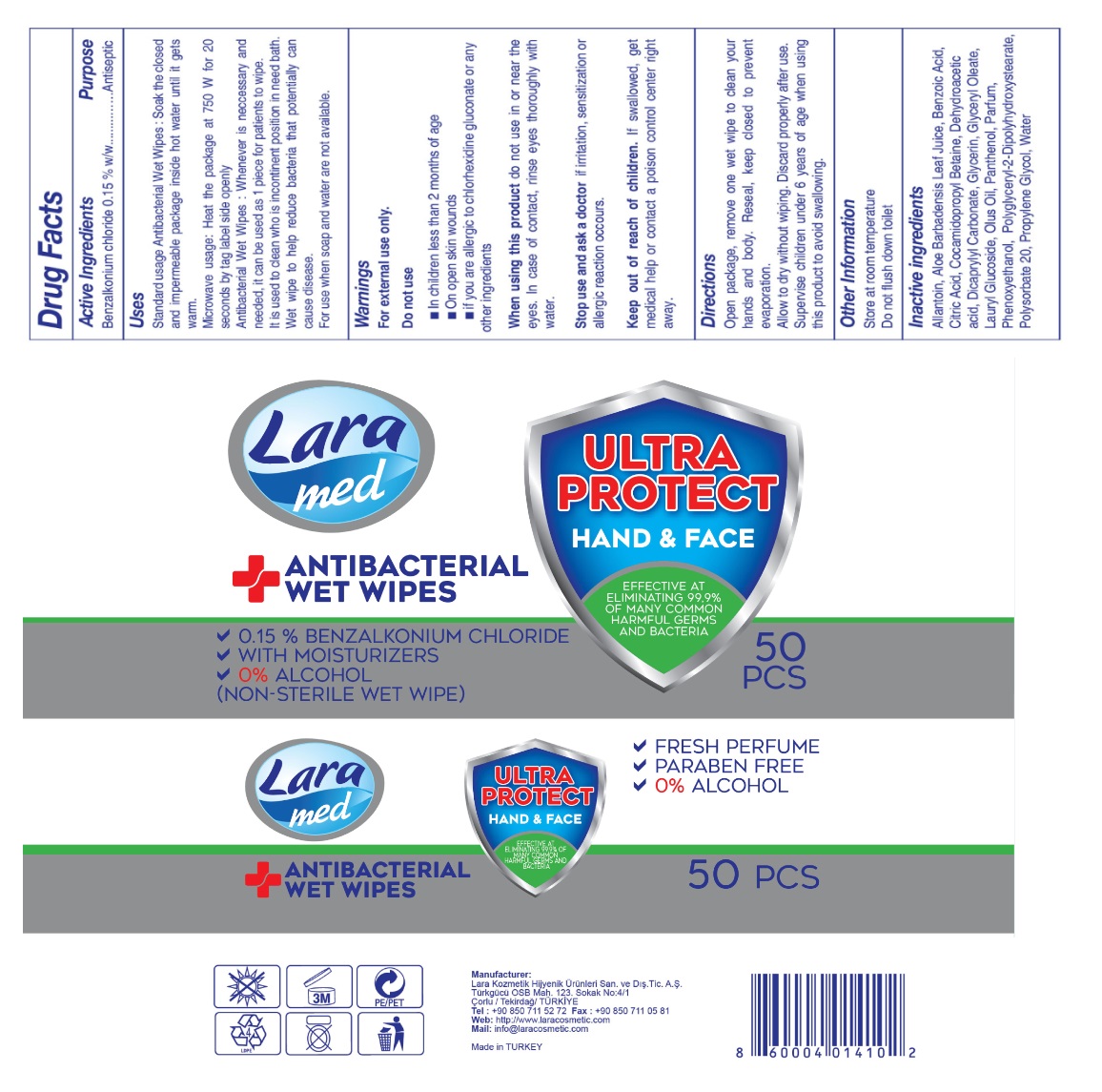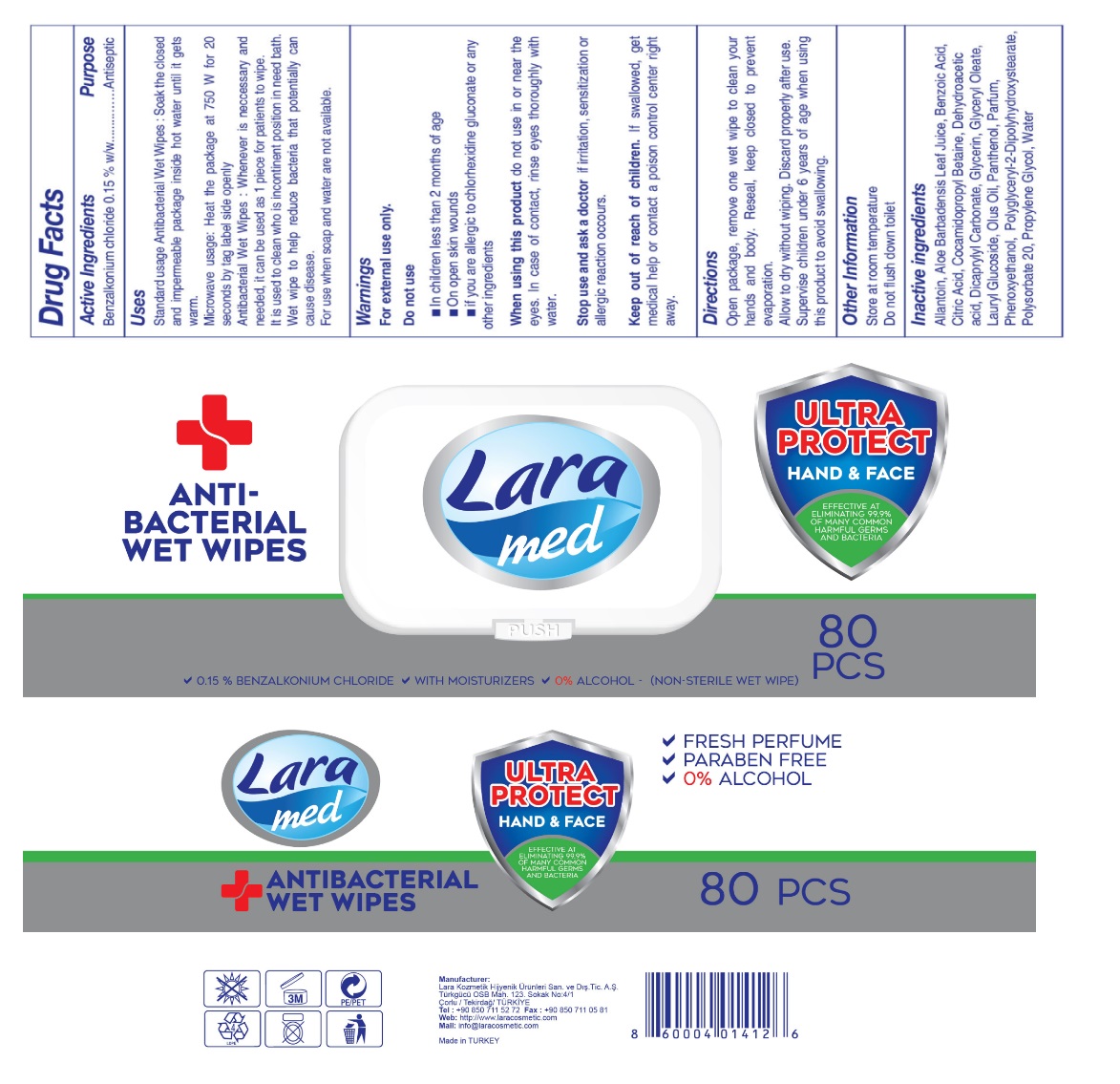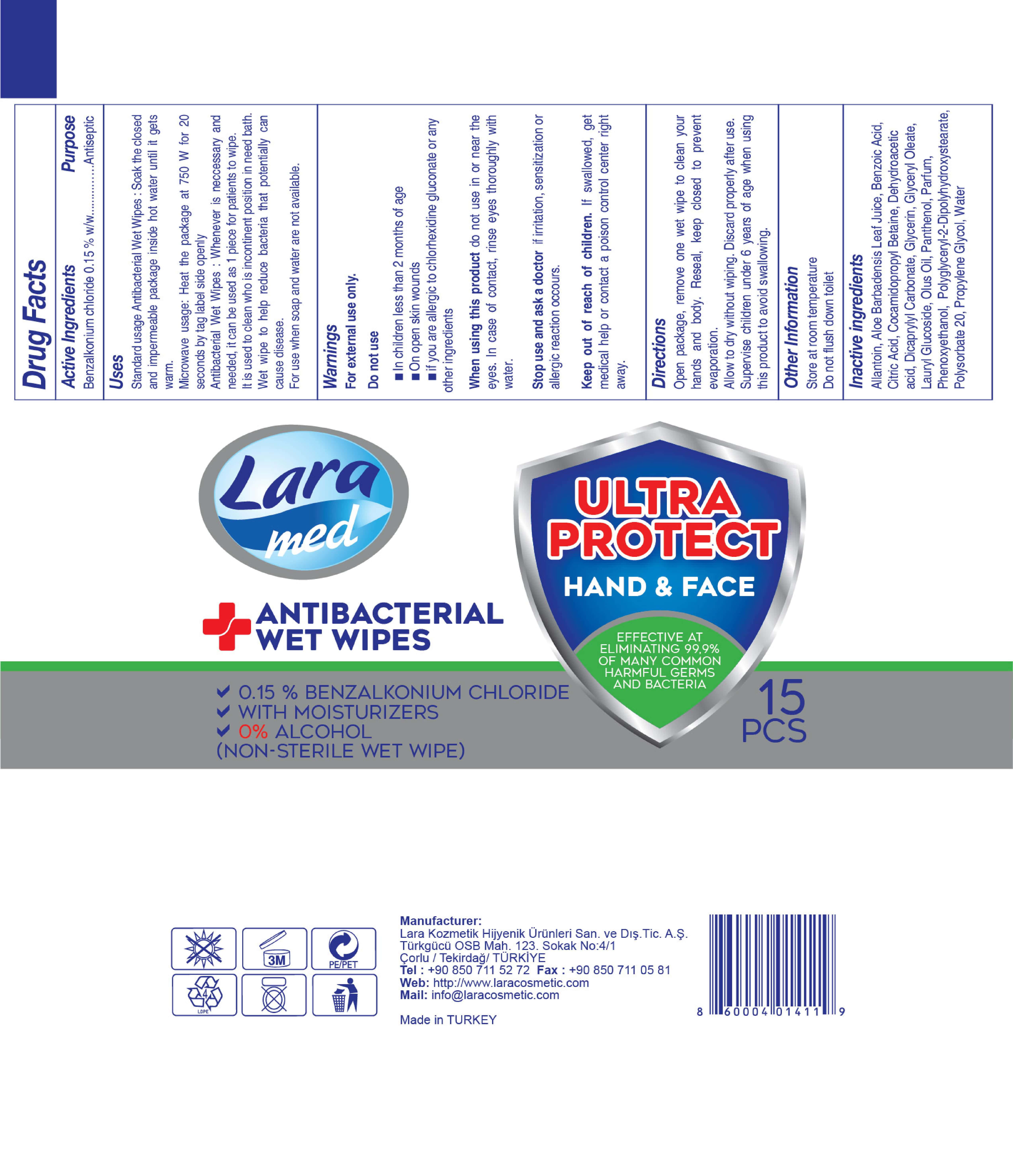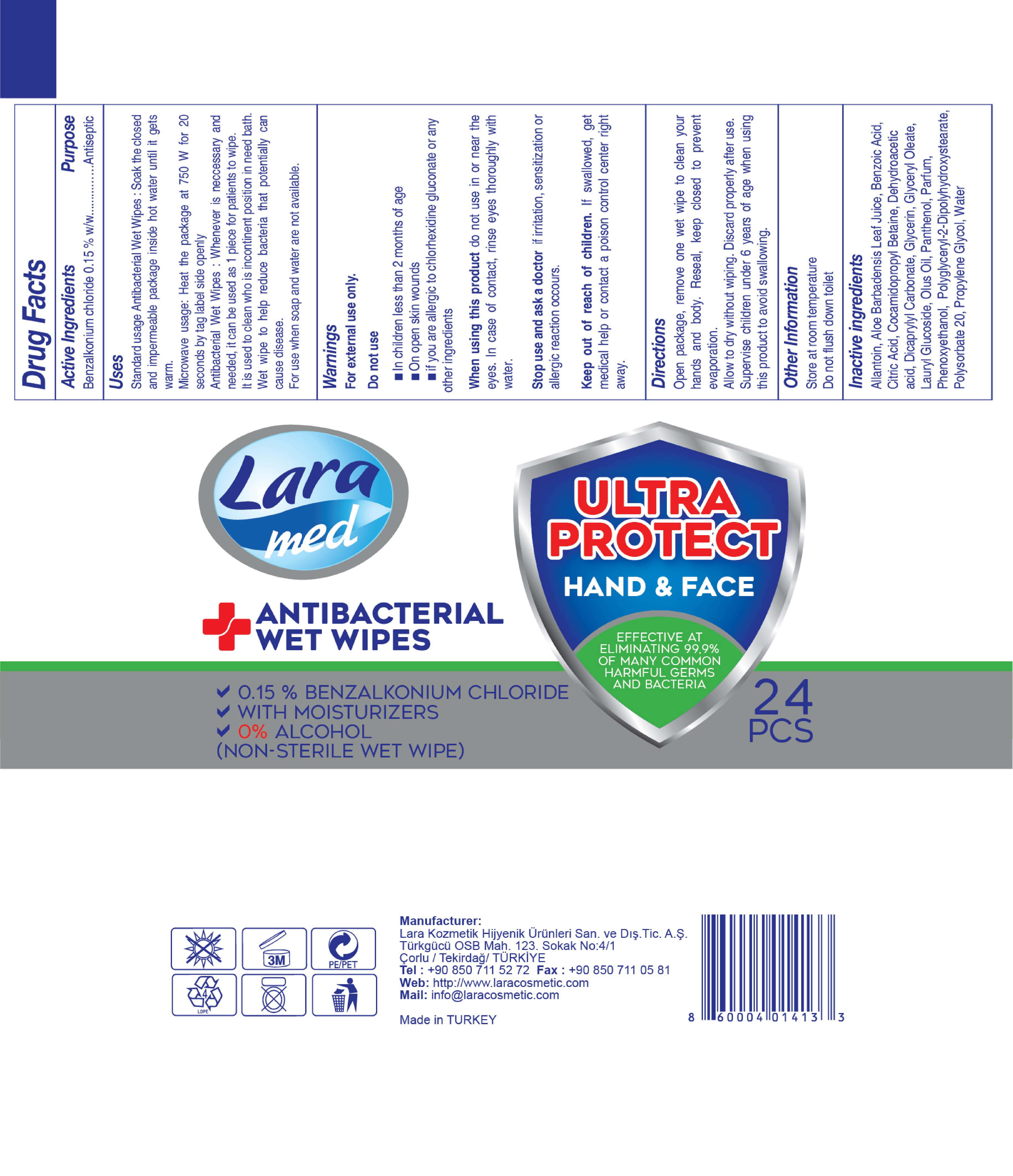 DRUG LABEL: LARA MED Antibacterial Wet Wipes
NDC: 86994-004 | Form: CLOTH
Manufacturer: LARA KOZMETIK HIJYENIK URUNLERI SANAYI VE DIS TICARET ANONIM SIRKETI
Category: otc | Type: HUMAN OTC DRUG LABEL
Date: 20201011

ACTIVE INGREDIENTS: BENZALKONIUM CHLORIDE 0.15 g/100 g
INACTIVE INGREDIENTS: DEHYDROACETIC ACID 0.0525 g/100 g; LAURYL GLUCOSIDE 0.06 g/100 g; PROPYLENE GLYCOL 0.0375 g/100 g; CITRIC ACID MONOHYDRATE 0.0225 g/100 g; ALLANTOIN 0.06 g/100 g; DICAPRYLYL CARBONATE 0.01 g/100 g; BENZOIC ACID 0.091 g/100 g; GLYCERIN 0.135 g/100 g; PHENOXYETHANOL 0.588 g/100 g; WATER 97.911 g/100 g; POLYSORBATE 20 0.225 g/100 g; ALOE VERA LEAF 0.0375 g/100 g; GLYCERYL OLEATE 0.01 g/100 g; POLYGLYCERYL-2 DIPOLYHYDROXYSTEARATE 0.06 g/100 g; DEXPANTHENOL 0.15 g/100 g; COCAMIDOPROPYL BETAINE 0.15 g/100 g

LARA MED Antibacterial Wet Wipes

This is a hand sanitizer manufactured according to the Temporary Policy for Preparation of Certain Alcohol-Based Hand Sanitizer Products During the Public Health Emergency (CoViD-19); Guidance for Industry.

The hand sanitizer is manufactured using only the following United States Pharmacopoeia (USP) grade ingredients in the preparation of the product (percentage in final product formulation) consistent with World Health Organization (WHO) recommendations:

1. Benzalkonium Chloride (USP or Food Chemical Codex (FCC) grade) (0.15%, weight/weight (w/w)) in an aqueous solution denatured Trade Bureau regulations in 27 CFR part 20
2. ALLANTOIN,
3. ALOE BARBADENSIS LEAF JUICE,
4. BENZOIC ACID,
5. CITRIC ACID,
6. COCAMIDOPROPYL BETAINE,
7. DEHYDROACETIC ACID,
8. DICAPRYLYL CARBONATE,
9. GLYCERIN,
10. GLYCERYL OLEATE,
11. LAURYL GLUCOSIDE,
12. OLUS OIL,
13. PANTHENOL,
14. PARFUM,
15. PHENOXYETHANOL,
16. POLYGLYCERYL-2-DIPOLYHYDROXYSTEARATE,
17. POLYSORBATE 20,
18. PROPYLENE GLYCOL,
19. WATER

The firm does not add other active or inactive ingredients. Different or additional ingredients may impact the quality and potency of the product.

Active Ingredient(s)

Benzalkonium Chloride 0.15% w/w. Purpose: Antiseptic

Purpose

Antiseptic, Hand Sanitizer

Use

Standard usage Antibacterial wet wipes; soak the closed and impermeable package inside hot water until it gets warm. Microwave usage: Heat the package at 750 W for seconds by lag label side openly.

Antibacterial Wet wipes: Whenever is necessary and needed, it can be used as 1 piece for patients to wipe.It is used to clean who is incontinent position in need bath.

Wet Wipe to help reduce bacteria that potentially can cause disease. For use when soap and water are not available.

Warnings

For external use only. If irritation occurs, discontinue use.

Do not use

- in children less than 2 months of age
- on open skin wounds
- if you are allergic to chlorhexidine gluconate or any other ingredients.

When using this product do not use in or near the eyes. In case of contact with eyes, rinse eyes thoroughly with water.
Stop use and ask a doctor if irritation or rash occurs. These may be signs of a serious condition.
Keep out of reach of children. If swallowed, get medical help or contact a Poison Control Center right away.

Stop use and ask a doctor if irritation, sensitization or allergic reaction occurs. These may be signs of a serious condition.

Keep out of reach of children. If swallowed, get medical help or contact a Poison Control Center right away.

Directions

- Open package, remove one wet wipes to clean your hands and body. Reseal, keep closed to prevent evaporation. Allow to dry without wiping. Discard properly after use.
- Supervise children under 6 years of age when using this product to avoid swallowing.

Other information

- Store at room temparature.
- Do not flush down toilet.

Inactive ingredients

ALLANTOIN, ALOE BARBADENSIS LEAF JUICE, BENZOIC ACID, CITRIC ACID, COCAMIDOPROPYL BETAINE, DEHYDROACETIC ACID, DICAPRYLYL CARBONATE, GLYCERIN, GLYCERYL OLEATE, LAURYL GLUCOSIDE, OLUS OIL, PANTHENOL, PARFUM, PHENOXYETHANOL, POLYGLYCERYL-2-DIPOLYHYDROXYSTEARATE, POLYSORBATE 20, PROPYLENE GLYCOL, WATER